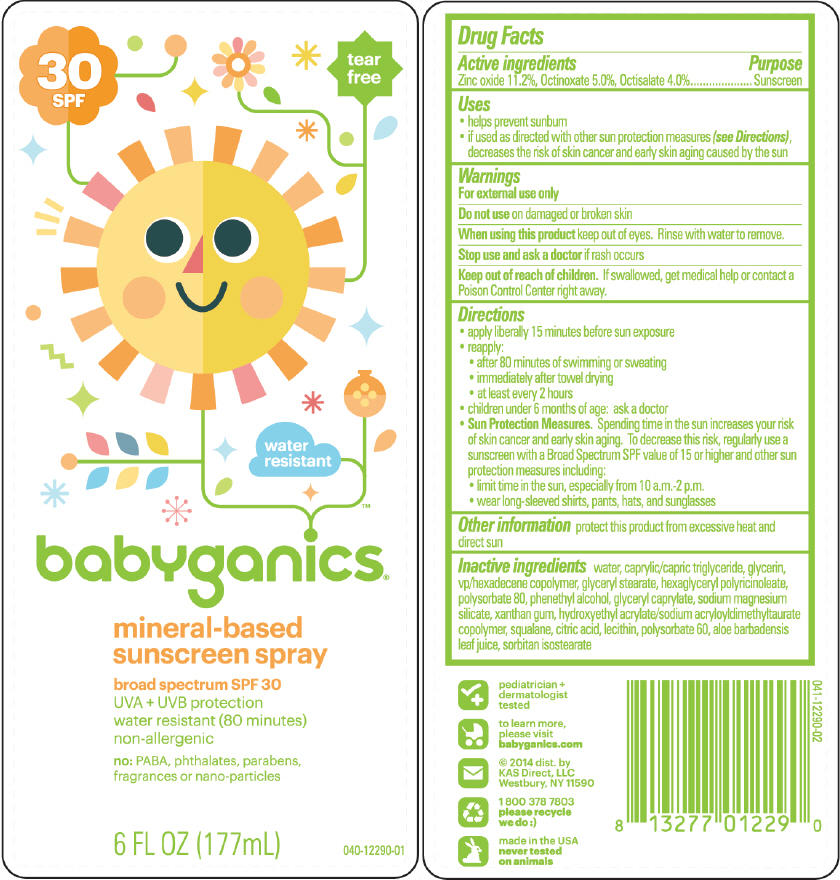 DRUG LABEL: BabyGanics Sunscreen 
NDC: 59062-1229 | Form: SPRAY
Manufacturer: KAS Direct LLC dba BabyGanics
Category: otc | Type: HUMAN OTC DRUG LABEL
Date: 20241219

ACTIVE INGREDIENTS: ZINC OXIDE 112 mg/1 mL; OCTINOXATE 50 mg/1 mL; OCTISALATE 40 mg/1 mL
INACTIVE INGREDIENTS: WATER; MEDIUM-CHAIN TRIGLYCERIDES; GLYCERIN; HEXADECYL POVIDONE; ALOE VERA LEAF; GLYCERYL MONOSTEARATE; POLYGLYCERYL-6 DIOLEATE; POLYSORBATE 80; PHENYLETHYL ALCOHOL; GLYCERYL MONOCAPRYLATE; SODIUM MAGNESIUM FLUOROSILICATE; XANTHAN GUM; HYDROXYETHYL ACRYLATE/SODIUM ACRYLOYLDIMETHYL TAURATE COPOLYMER (100000 MPA.S AT 1.5%); SQUALANE; CITRIC ACID MONOHYDRATE; SOYBEAN LECITHIN; POLYSORBATE 60; SORBITAN ISOSTEARATE

babyganics® Sunscreen Spray 30 SPF

Drug Facts

Active ingredients

Octinoxate 5.0%, Octisalate 4.0%, Zinc oxide 11.2%

Purpose

Sunscreen

Uses

- helps prevent sunburn
- if used as directed with other sun protection measures (see Directions), decreases the risk of skin cancer and early skin aging caused by the sun

Warnings

For external use only

Do not use on damaged or broken skin

When using this product keep out of eyes. Rinse with water to remove.

Stop use and ask a doctor if rash occurs

Keep out of reach of children. If swallowed, get medical help or contact a Poison Control Center right away.

Directions

- apply liberally 15 minutes before sun exposure
- reapply:
  - after 80 minutes of swimming or sweating
  - immediately after towel drying
  - at least every 2 hours
- children under 6 months of age: ask a doctor
- Sun Protection Measures. Spending time in the sun increases your risk of skin cancer and early skin aging. To decrease this risk, regularly use a sunscreen with a Broad Spectrum SPF value of 15 or higher and other sun protection measures including:
  - limit time in the sun, especially from 10 a.m.-2 p.m.
  - wear long-sleeved shirts, pants, hats, and sunglasses

Other information

protect this product from excessive heat and direct sun

Inactive ingredients

water, caprylic/capric triglyceride, glycerin, vp/hexadecene copolymer, aloe barbadensis leaf juice, glyceryl stearate, hexaglyceryl polyricinoleate, polysorbate 80, phenethyl alcohol, glyceryl caprylate, sodium magnesium silicate, xanthan gum, hydroxyethyl acrylate/sodium acryloyldimethyltaurate copolymer, squalane, citric acid, lecithin, polysorbate 60, sorbitan isostearate.

Dist. by:
KAS Direct, LLC.
Hicksville, NY 11801

PRINCIPAL DISPLAY PANEL - 177 mL Bottle Label

30
SPF

tear
free

water
resistant

babyganics®

mineral-based
sunscreen spray

broad spectrum SPF 30
UVA + UVB protection
water resistant (80 minutes)
non-allergenic

no: PABA, phthalates, parabens,
fragrances or nano-particles

6 FL OZ (177mL)

040-12290-01